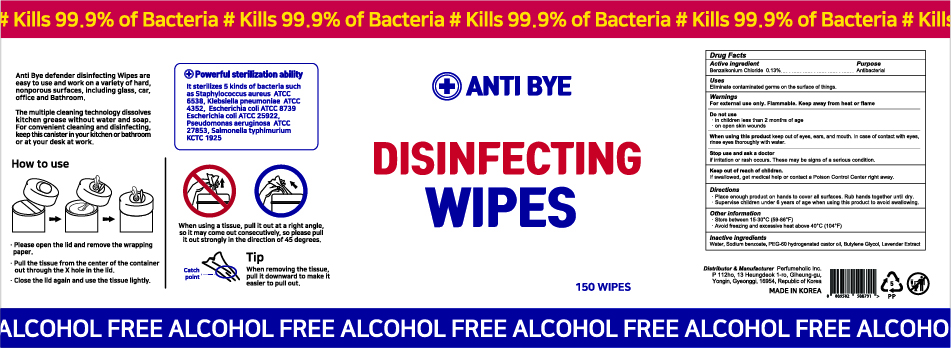 DRUG LABEL: ANTI BYE DISINFECTING WIPES
NDC: 75773-013 | Form: CLOTH
Manufacturer: Perfumeholic Inc
Category: otc | Type: HUMAN OTC DRUG LABEL
Date: 20201203

ACTIVE INGREDIENTS: BENZALKONIUM CHLORIDE 0.013 1/1 1
INACTIVE INGREDIENTS: PEG-60 HYDROGENATED CASTOR OIL; BUTYLENE GLYCOL; WATER; SODIUM BENZOATE; LAVENDER OIL

Perfumeholic Inc | ANTI BYE DISINFECTING WIPES | 75773-013-15 | 150 WIPES